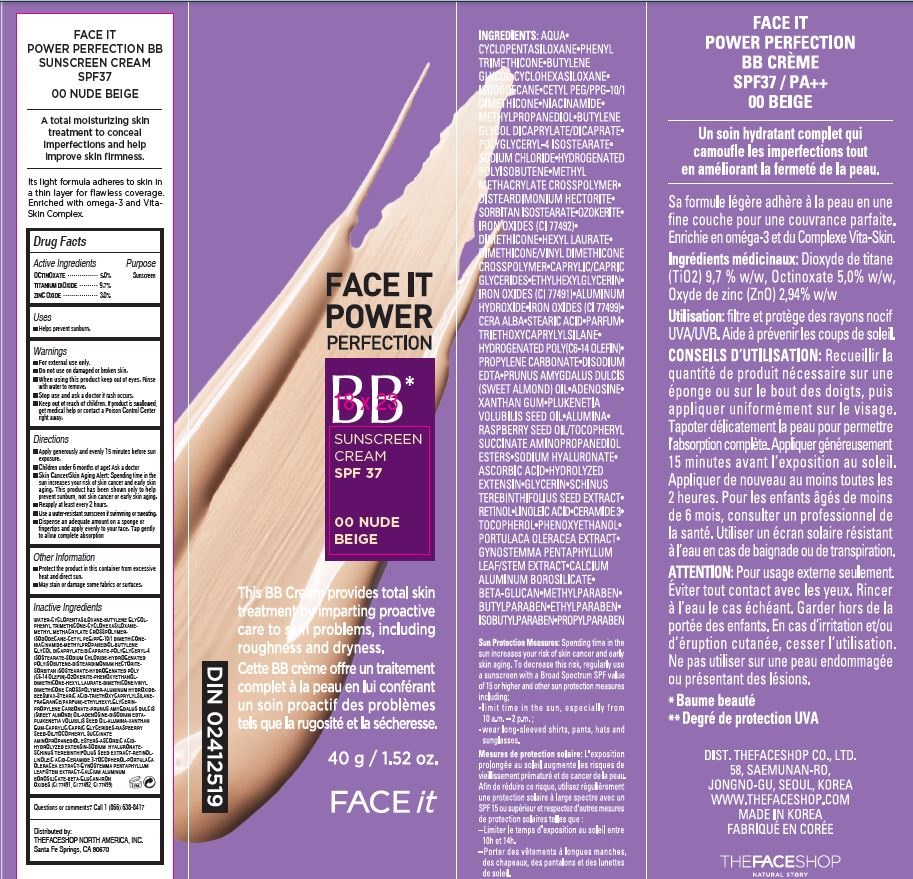 DRUG LABEL: FACE IT POWER PERFECTION BB 00
NDC: 51523-842 | Form: CREAM
Manufacturer: THEFACESHOP Co., Ltd.
Category: otc | Type: HUMAN OTC DRUG LABEL
Date: 20141120

ACTIVE INGREDIENTS: OCTINOXATE 2 g/40 g; TITANIUM DIOXIDE 3.9 g/40 g; ZINC OXIDE 1.2 g/40 g
INACTIVE INGREDIENTS: WATER

FACE IT POWER PERFECTION BB CREAM 00 32800842

Active Ingredients

OCTINOXATE • • • • • • • • • • • • • 5.0%
TITANIUM DIOXIDE • • • • • • • • • 9.7%
ZINC OXIDE • • • • • • • • • • • • • • 3.0%

Purpose

Sunscreen

Sunscreen

Sunscreen

Warnings

For external use only.

Do not use on damaged or broken skin.

When using this product keep out of eyes. Rinse with water to remove.

Stop use and ask a doctor if rash occurs.

Keep out of reach of children. If product is swallowed, get medical help or contact a Poison Control Center right away.

Directions

Apply generously and evenly 15 minutes before sun exposure.
Children under 6 months of age: Ask a doctor
Skin Cancer/Skin Aging Alert: Spending time in the sun increases your risk of skin cancer and early skin. aging. This product has been shown only to help prevent sunburn, not skin cancer or early skin aging.
Reapply at least every 2 hours
Use a water-resistant sunscreen if swimming or sweating.
Dispense an adequate amount on a sponge or fingertips and apply evenly to your face. Tap gently to allow complete absorption.

Other Information

Protect the product in this container from excessive heat and direct sun.

May stain or damage some fabrics or surfaces.

Inactive Ingredients

WATER•CYCLOPENTASILOXANE•BUTYLENE GLYCOL•
PHENYL TRIMETHICONE•CYCLOHEXASILOXANE•
METHYL METHACRYLATE CROSSPOLYMER•
ISODODECANE•CETYL PEG/PPG-10/1 DIMETHICONE•
NIACINAMIDE•METHYLPROPANEDIOL•BUTYLENE
GLYCOL DICAPRYLATE/DICAPRATE•POLYGLYCERYL-4
ISOSTEARATE•SODIUM CHLORIDE•HYDROGENATED
POLYISOBUTENE•DISTEARDIMONIUM HECTORITE•
SORBITAN ISOSTEARATE•HYDROGENATED POLY
(C6-14 OLEFIN)•OZOKERITE•PHENOXYETHANOL•
DIMETHICONE•HEXYL LAURATE•DIMETHICONE/VINYL
DIMETHICONE CROSSPOLYMER•ALUMINUM HYDROXIDE•
BEESWAX•STEARIC ACID•TRIETHOXYCAPRYLYLSILANE•
FRAGRANCE(PARFUM)•ETHYLHEXYLGLYCERIN•
PROPYLENE CARBONATE•PRUNUS AMYGDALUS DULCIS
(SWEET ALMOND) OIL•ADENOSINE•DISODIUM EDTA•
PLUKENETIA VOLUBILIS SEED OIL•ALUMINA•XANTHAN
GUM•CAPRYLIC/CAPRIC GLYCERIDES•RASPBERRY
SEED•OIL/TOCOPHERYL SUCCINATE
AMINOPROPANEDIOL ESTERS•ASCORBIC ACID•
HYDROLYZED EXTENSIN•SODIUM HYALURONATE•
SCHINUS TEREBINTHIFOLIUS SEED EXTRACT•RETINOL•
LINOLEIC ACID•CERAMIDE 3•TOCOPHEROL•PORTULACA
OLERACEA EXTRACT•GYNOSTEMMA PENTAPHYLLUM
LEAF/STEM EXTRACT•CALCIUM ALUMINUM
BOROSILICATE•BETA-GLUCAN•IRON
OXIDES (CI 77491, CI 77492, CI 77499)

Questions or comments? Call 1 (866) 638-8417

Distributed by:

THEFACESHOP NORTH AMERICA, INC.
Santa Fe Springs, CA 90670

PACKAGE LABEL

FACE IT POWER PERFECTION BB

SUNSCREEN CREAM SPF 37

00 NUDE BEIGE

40 g / 1.52 oz.